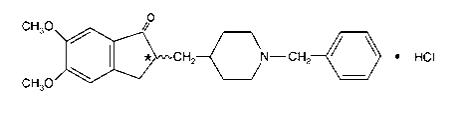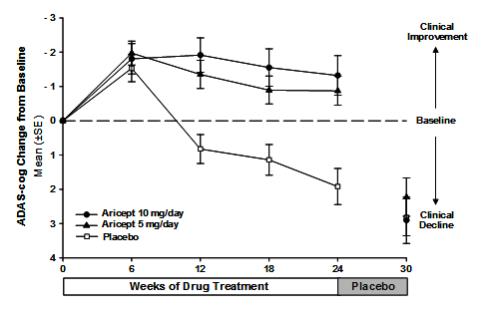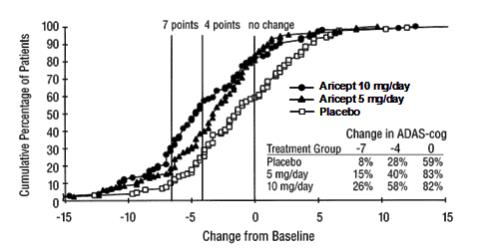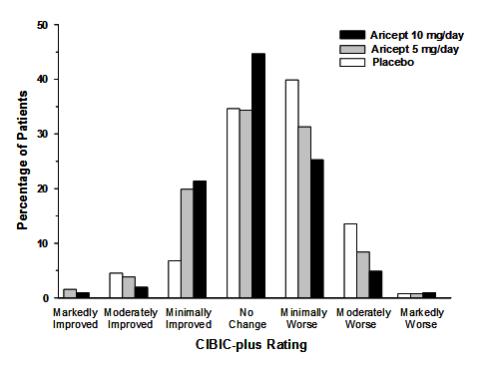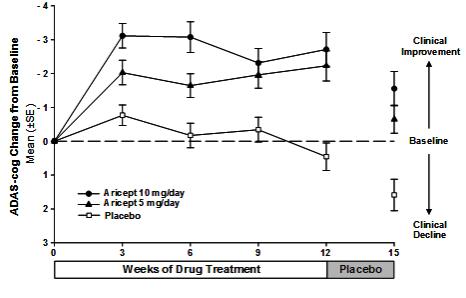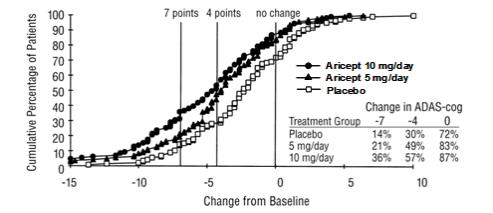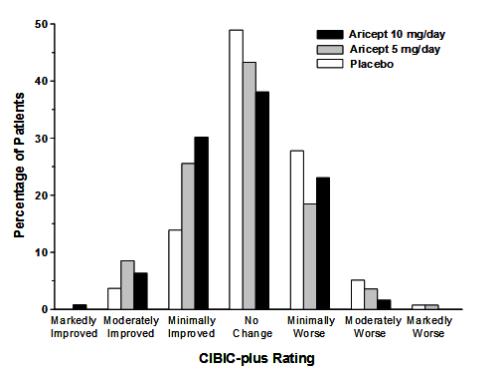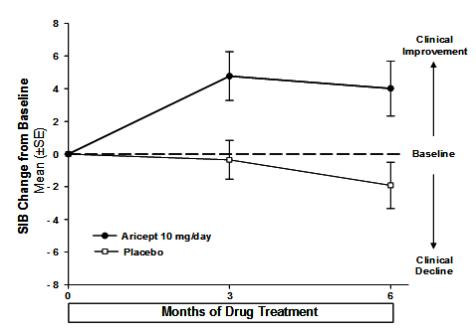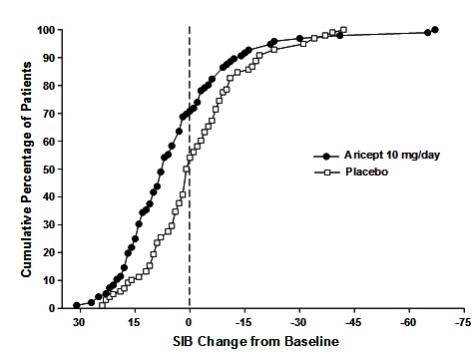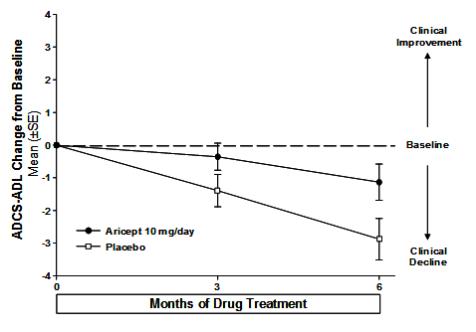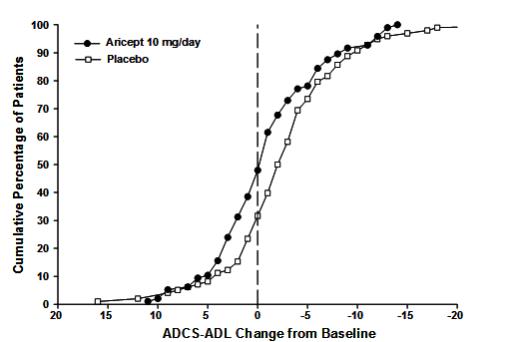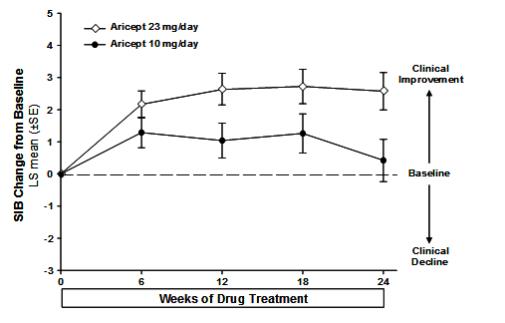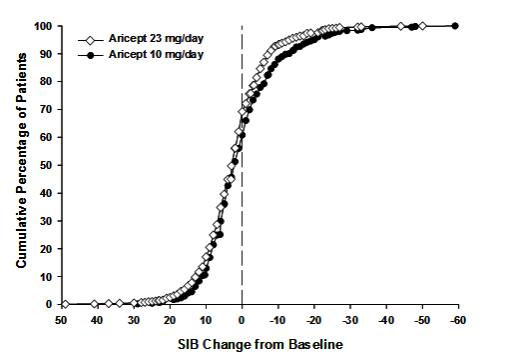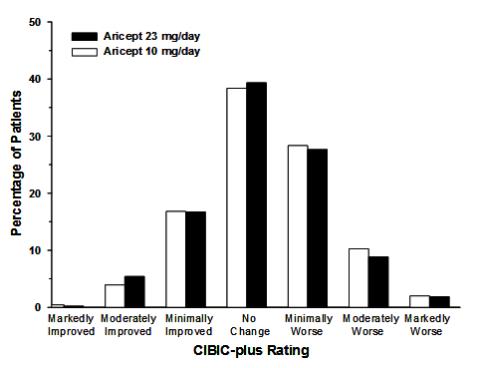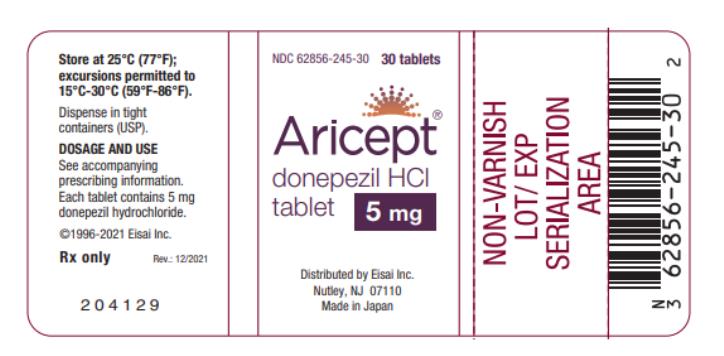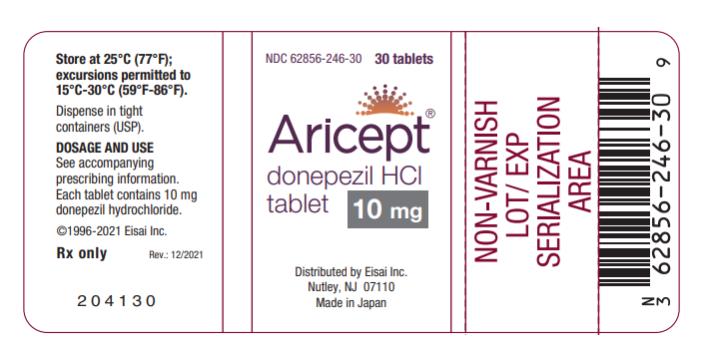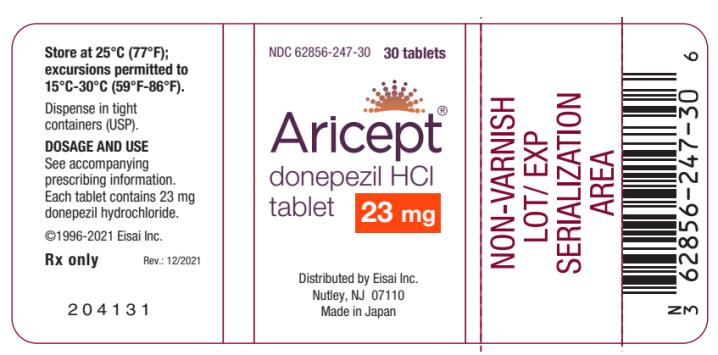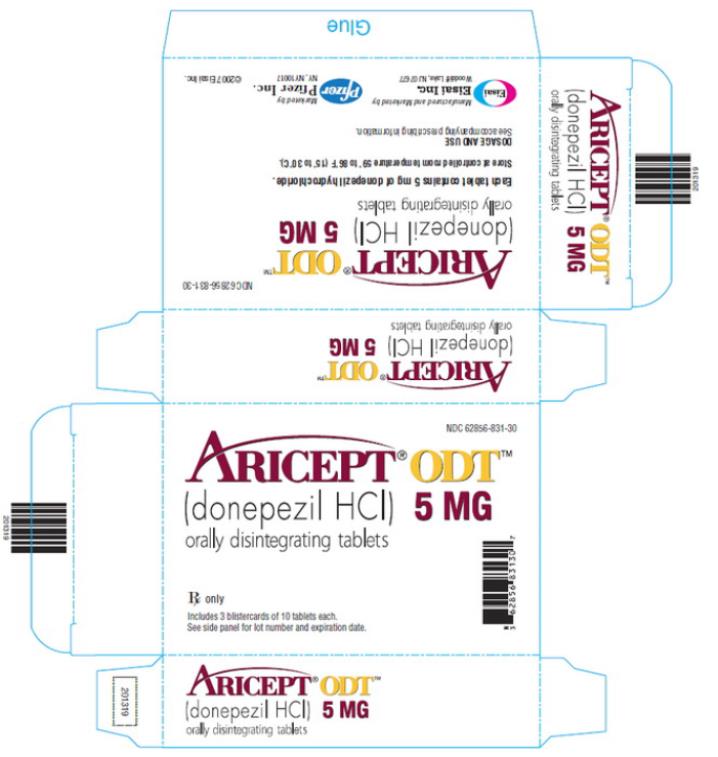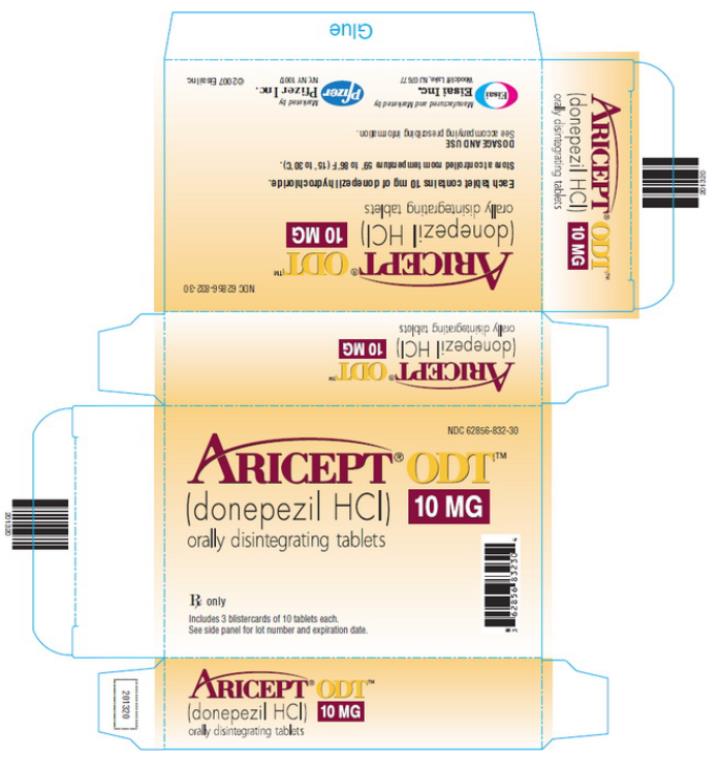 DRUG LABEL: Aricept
NDC: 62856-245 | Form: TABLET, FILM COATED
Manufacturer: Eisai Inc.
Category: prescription | Type: HUMAN PRESCRIPTION DRUG LABEL
Date: 20211201

ACTIVE INGREDIENTS: DONEPEZIL HYDROCHLORIDE 5 mg/1 1
INACTIVE INGREDIENTS: LACTOSE MONOHYDRATE; STARCH, CORN; CELLULOSE, MICROCRYSTALLINE; MAGNESIUM STEARATE; TALC; POLYETHYLENE GLYCOL 8000; HYPROMELLOSES; TITANIUM DIOXIDE; HYDROXYPROPYL CELLULOSE (90000 WAMW)

HIGHLIGHTS OF PRESCRIBING INFORMATION

These highlights do not include all the information needed to use ARICEPT safely and effectively. See full prescribing information for ARICEPT.
ARICEPT® (donepezil hydrochloride) tablets, for oral use
ARICEPT ODT (donepezil hydrochloride) orally disintegrating tablets
Initial U.S. Approval: 1996

1 INDICATIONS AND USAGE

ARICEPT is an acetylcholinesterase inhibitor indicated for the treatment of dementia of the Alzheimer’s type. Efficacy has been demonstrated in patients with mild, moderate, and severe Alzheimer’s Disease (1)

2 DOSAGE AND ADMINISTRATION

- Mild to Moderate Alzheimer’s Disease: 5 mg to 10 mg once daily (2.1)
- Moderate to Severe Alzheimer’s Disease: 10 mg to 23 mg once daily (2.2)

3 DOSAGE FORMS AND STRENGTHS

- Tablets: 5 mg, 10 mg, and 23 mg (3)
- Orally Disintegrating Tablets (ODT): 5 mg and 10 mg (3)

4 CONTRAINDICATIONS

Known hypersensitivity to donepezil hydrochloride or to piperidine derivatives (4)

5 WARNINGS AND PRECAUTIONS

- Cholinesterase inhibitors are likely to exaggerate succinylcholine-type muscle relaxation during anesthesia (5.1)
- Cholinesterase inhibitors may have vagotonic effects on the sinoatrial and atrioventricular nodes manifesting as bradycardia or heart block (5.2)
- ARICEPT can cause vomiting. Patients should be observed closely at initiation of treatment and after dose increases (5.3)
- Patients should be monitored closely for symptoms of active or occult gastrointestinal (GI) bleeding, especially those at increased risk for developing ulcers (5.4)
- The use of ARICEPT in a dose of 23 mg once daily is associated with weight loss (5.5)
- Cholinomimetics may cause bladder outflow obstructions (5.6)
- Cholinomimetics are believed to have some potential to cause generalized convulsions (5.7)
- Cholinesterase inhibitors should be prescribed with care to patients with a history of asthma or obstructive pulmonary disease (5.8)

6 ADVERSE REACTIONS

Most common adverse reactions in clinical studies of ARICEPT are nausea, diarrhea, insomnia, vomiting, muscle cramps, fatigue, and anorexia (6.1)

To report SUSPECTED ADVERSE REACTIONS, contact Eisai Inc. at 1-888-274-2378 (fax 1-201-746-3207) or FDA at 1-800-FDA-1088 or www.fda.gov/medwatch.

7 DRUG INTERACTIONS

- Cholinesterase inhibitors have the potential to interfere with the activity of anticholinergic medications (7.1)
- A synergistic effect may be expected with concomitant administration of succinylcholine, similar neuromuscular blocking agents, or cholinergic agonists (7.2)

8 USE IN SPECIFIC POPULATIONS

Pregnancy: Based on animal data, may cause fetal harm (8.1)

FULL PRESCRIBING INFORMATION

1 INDICATIONS AND USAGE

ARICEPT is indicated for the treatment of dementia of the Alzheimer’s type. Efficacy has been demonstrated in patients with mild, moderate, and severe Alzheimer’s disease.

2 DOSAGE AND ADMINISTRATION

2.1 Dosing in Mild to Moderate Alzheimer’s Disease

The recommended starting dosage of ARICEPT is 5 mg administered once per day in the evening, just prior to retiring. The maximum recommended dosage of ARICEPT in patients with mild to moderate Alzheimer’s disease is 10 mg per day. A dose of 10 mg should not be administered until patients have been on a daily dose of 5 mg for 4 to 6 weeks.

2.2 Dosing in Moderate to Severe Alzheimer’s Disease

The recommended starting dosage of ARICEPT is 5 mg administered once per day in the evening, just prior to retiring. The maximum recommended dosage of ARICEPT in patients with moderate to severe Alzheimer’s disease is 23 mg per day. A dose of 10 mg should not be administered until patients have been on a daily dose of 5 mg for 4 to 6 weeks. A dose of 23 mg per day should not be administered until patients have been on a daily dose of 10 mg for at least 3 months.

2.3 Administration Information

ARICEPT should be taken in the evening, just prior to retiring. ARICEPT can be taken with or without food.

The ARICEPT 23 mg tablet should not be split, crushed, or chewed.

Allow ARICEPT ODT to dissolve on the tongue and follow with water.

3 DOSAGE FORMS AND STRENGTHS

ARICEPT is supplied as film-coated, round tablets containing 5 mg, 10 mg, or 23 mg of donepezil hydrochloride.

- The 5 mg tablets are white. The strength, in mg (5), is debossed on one side and ARICEPT is debossed on the other side.
- The 10 mg tablets are yellow. The strength, in mg (10), is debossed on one side and ARICEPT is debossed on the other side.
- The 23 mg tablets are reddish. The strength, in mg (23), is debossed on one side, and ARICEPT is debossed on the other side.

ARICEPT ODT is supplied as round tablets containing either 5 mg or 10 mg of donepezil hydrochloride.

- The 5 mg orally disintegrating tablets are white. The strength, in mg (5), is debossed on one side and ARICEPT is debossed on the other side.
- The 10 mg orally disintegrating tablets are yellow. The strength, in mg (10), is debossed on one side and ARICEPT is debossed on the other side.

4 CONTRAINDICATIONS

ARICEPT is contraindicated in patients with known hypersensitivity to donepezil hydrochloride or to piperidine derivatives.

5 WARNINGS AND PRECAUTIONS

5.1 Anesthesia

ARICEPT, as a cholinesterase inhibitor, is likely to exaggerate succinylcholine-type muscle relaxation during anesthesia.

5.2 Cardiovascular Conditions

Because of their pharmacological action, cholinesterase inhibitors may have vagotonic effects on the sinoatrial and atrioventricular nodes. This effect may manifest as bradycardia or heart block in patients both with and without known underlying cardiac conduction abnormalities. Syncopal episodes have been reported in association with the use of ARICEPT.

5.3 Nausea and Vomiting

ARICEPT, as a predictable consequence of its pharmacological properties, has been shown to produce diarrhea, nausea, and vomiting. These effects, when they occur, appear more frequently with the 10 mg/day dose than with the 5 mg/day dose, and more frequently with the 23 mg dose than with the 10 mg dose. Specifically, in a controlled trial that compared a dose of 23 mg/day to 10 mg/day in patients who had been treated with donepezil 10 mg/day for at least three months, the incidence of nausea in the 23 mg group was markedly greater than in the patients who continued on 10 mg/day (11.8% vs. 3.4%, respectively), and the incidence of vomiting in the 23 mg group was markedly greater than in the 10 mg group (9.2% vs. 2.5%, respectively). The percent of patients who discontinued treatment due to vomiting in the 23 mg group was markedly higher than in the 10 mg group (2.9% vs. 0.4%, respectively).

Although in most cases, these effects have been transient, sometimes lasting one to three weeks, and have resolved during continued use of ARICEPT, patients should be observed closely at the initiation of treatment and after dose increases.

5.4 Peptic Ulcer Disease and GI Bleeding

Through their primary action, cholinesterase inhibitors may be expected to increase gastric acid secretion due to increased cholinergic activity. Therefore, patients should be monitored closely for symptoms of active or occult gastrointestinal bleeding, especially those at increased risk for developing ulcers, e.g., those with a history of ulcer disease or those receiving concurrent nonsteroidal anti-inflammatory drugs (NSAIDs). Clinical studies of ARICEPT in a dose of 5 mg/day to 10 mg/day have shown no increase, relative to placebo, in the incidence of either peptic ulcer disease or gastrointestinal bleeding. Results of a controlled clinical study with 23 mg/day showed an increase, relative to 10 mg/day, in the incidence of peptic ulcer disease (0.4% vs. 0.2%) and gastrointestinal bleeding from any site (1.1% vs. 0.6%).

5.5 Weight Loss

Weight loss was reported as an adverse reaction in 4.7% of patients assigned to ARICEPT in a dose of 23 mg/day compared to 2.5% of patients assigned to 10 mg/day. Compared to their baseline weights, 8.4% of patients taking 23 mg/day were found to have a weight decrease of ≥ 7% by the end of the study, while 4.9% of patients taking 10 mg/day were found to have weight loss of ≥ 7% at the end of the study.

5.6 Genitourinary Conditions

Although not observed in clinical trials of ARICEPT, cholinomimetics may cause bladder outflow obstruction.

5.7 Neurological Conditions: Seizures

Cholinomimetics are believed to have some potential to cause generalized convulsions. However, seizure activity also may be a manifestation of Alzheimer’s disease.

5.8 Pulmonary Conditions

Because of their cholinomimetic actions, cholinesterase inhibitors should be prescribed with care to patients with a history of asthma or obstructive pulmonary disease.

6 ADVERSE REACTIONS

The following serious adverse reactions are described below and elsewhere in the labeling:

- Cardiovascular Conditions [see Warnings and Precautions (5.2)]
- Nausea and Vomiting [see Warnings and Precautions (5.3)]
- Peptic Ulcer Disease and GI Bleeding [see Warnings and Precautions (5.4)]
- Weight Loss [see Warnings and Precautions (5.5)]
- Genitourinary Conditions [see Warnings and Precautions (5.6)]
- Neurological Conditions: Seizures [see Warnings and Precautions (5.7)]
- Pulmonary Conditions [see Warnings and Precautions (5.8)]

6.1 Clinical Trials Experience

Because clinical trials are conducted under widely varying conditions, adverse reaction rates observed in the clinical trials of a drug cannot be directly compared to rates in the clinical trials of another drug and may not reflect the rates observed in practice.

ARICEPT has been administered to over 1,700 individuals during clinical trials worldwide. Approximately 1200 of these patients have been treated for at least 3 months and more than 1,000 patients have been treated for at least 6 months. Controlled and uncontrolled trials in the United States included approximately 900 patients. In regards to the highest dose of 10 mg/day, this population includes 650 patients treated for 3 months, 475 patients treated for 6 months, and 116 patients treated for over 1 year. The range of patient exposure is from 1 to 1,214 days.

Mild to Moderate Alzheimer’s Disease

Adverse Reactions Leading to Discontinuation
The rates of discontinuation from controlled clinical trials of ARICEPT due to adverse reactions for the ARICEPT 5 mg/day treatment groups were comparable to those of placebo treatment groups at approximately 5%. The rate of discontinuation of patients who received 7-day escalations from 5 mg/day to 10 mg/day was higher at 13%.

The most common adverse reactions leading to discontinuation, defined as those occurring in at least 2% of patients and at twice or more the incidence seen in placebo patients, are shown in Table 1.

Table 1. Most Common Adverse Reactions Leading to
Discontinuation in Patients with Mild to Moderate
Alzheimer’s Disease
Adverse Reaction | Placebo (n=355) % | 5 mg/day ARICEPT (n=350) % | 10 mg/day ARICEPT (n=315) %
Nausea | 1 | 1 | 3
Diarrhea | 0 | <1 | 3
Vomiting | <1 | <1 | 2

Most Common Adverse Reactions

The most common adverse reactions, defined as those occurring at a frequency of at least 5% in patients receiving 10 mg/day and twice the placebo rate, are largely predicted by ARICEPT’s cholinomimetic effects. These include nausea, diarrhea, insomnia, vomiting, muscle cramp, fatigue, and anorexia. These adverse reactions were often transient, resolving during continued ARICEPT treatment without the need for dose modification.

There is evidence to suggest that the frequency of these common adverse reactions may be affected by the rate of titration. An open-label study was conducted with 269 patients who received placebo in the 15- and 30-week studies. These patients were titrated to a dose of 10 mg/day over a 6-week period. The rates of common adverse reactions were lower than those seen in patients titrated to 10 mg/day over one week in the controlled clinical trials and were comparable to those seen in patients on 5 mg/day.

See Table 2 for a comparison of the most common adverse reactions following one and six week titration regimens.

Table 2. Comparison of Rates of Adverse Reactions in Mild to Moderate
Patients Titrated to 10 mg/day over 1 and 6 Weeks
 | No titration |  | One week titration | Six week titration
Adverse Reaction | Placebo (n=315) % | 5 mg/day (n=311) % | 10 mg/day (n=315) % | 10 mg/day (n=269) %
Nausea | 6 | 5 | 19 | 6
Diarrhea | 5 | 8 | 15 | 9
Insomnia | 6 | 6 | 14 | 6
Fatigue | 3 | 4 | 8 | 3
Vomiting | 3 | 3 | 8 | 5
Muscle cramps | 2 | 6 | 8 | 3
Anorexia | 2 | 3 | 7 | 3

Table 3 lists adverse reactions that occurred in at least 2% of patients in pooled placebo-controlled trials who received either ARICEPT 5 mg or 10 mg and for which the rate of occurrence was greater for patients treated with ARICEPT than with placebo. In general, adverse reactions occurred more frequently in female patients and with advancing age.

Table 3. Adverse Reactions in Pooled Placebo-Controlled Clinical Trials in Mild to Moderate Alzheimer’s Disease
Adverse Reaction | Placebo (n=355) % | ARICEPT (n=747) %
Percent of Patients with any Adverse Reaction | 72 | 74
Nausea | 6 | 11
Diarrhea | 5 | 10
Headache | 9 | 10
Insomnia | 6 | 9
Pain, various locations | 8 | 9
Dizziness | 6 | 8
Accident | 6 | 7
Muscle Cramps | 2 | 6
Fatigue | 3 | 5
Vomiting | 3 | 5
Anorexia | 2 | 4
Ecchymosis | 3 | 4
Abnormal Dreams | 0 | 3
Depression | <1 | 3
Weight Loss | 1 | 3
Arthritis | 1 | 2
Frequent Urination | 1 | 2
Somnolence | <1 | 2
Syncope | 1 | 2

Severe Alzheimer’s Disease (ARICEPT 5 mg/day and 10 mg/day)

ARICEPT has been administered to over 600 patients with severe Alzheimer’s disease during clinical trials of at least 6 months duration, including three double-blind, placebo-controlled trials, two of which had an open label extension.

Adverse Reactions Leading to Discontinuation

The rates of discontinuation from controlled clinical trials of ARICEPT due to adverse reactions for the ARICEPT patients were approximately 12% compared to 7% for placebo patients. The most common adverse reactions leading to discontinuation, defined as those occurring in at least 2% of ARICEPT patients and at twice or more the incidence seen in placebo, were anorexia (2% vs. 1% placebo), nausea (2% vs. <1% placebo), diarrhea (2% vs. 0% placebo), and urinary tract infection (2% vs. 1% placebo).

Most Common Adverse Reactions

The most common adverse reactions, defined as those occurring at a frequency of at least 5% in patients receiving ARICEPT and at twice or more the placebo rate, are largely predicted by ARICEPT’s cholinomimetic effects. These include diarrhea, anorexia, vomiting, nausea, and ecchymosis. These adverse reactions were often transient, resolving during continued ARICEPT treatment without the need for dose modification.

Table 4 lists adverse reactions that occurred in at least 2% of patients in pooled placebo-controlled trials who received ARICEPT 5 mg or 10 mg and for which the rate of occurrence was greater for patients treated with ARICEPT than with placebo.

Table 4. Adverse Reactions in Pooled Controlled Clinical Trials in Severe Alzheimer’s Disease
Body System/Adverse Reaction | Placebo (n=392) % | ARICEPT (n=501) %
Percent of Patients with any Adverse Reaction | 73 | 81
Accident | 12 | 13
Infection | 9 | 11
Diarrhea | 4 | 10
Anorexia | 4 | 8
Vomiting | 4 | 8
Nausea | 2 | 6
Insomnia | 4 | 5
Ecchymosis | 2 | 5
Headache | 3 | 4
Hypertension | 2 | 3
Pain | 2 | 3
Back Pain | 2 | 3
Eczema | 2 | 3
Hallucinations | 1 | 3
Hostility | 2 | 3
Increase in Creatine Phosphokinase | 1 | 3
Nervousness | 2 | 3
Fever | 1 | 2
Chest Pain | <1 | 2
Confusion | 1 | 2
Dehydration | 1 | 2
Depression | 1 | 2
Dizziness | 1 | 2
Emotional Lability | 1 | 2
Hemorrhage | 1 | 2
Hyperlipemia | <1 | 2
Personality Disorder | 1 | 2
Somnolence | 1 | 2
Syncope | 1 | 2
Urinary Incontinence | 1 | 2

Moderate to Severe Alzheimer’s Disease (ARICEPT 23 mg/day)

ARICEPT 23 mg/day has been administered to over 1300 individuals globally in clinical trials. Approximately 1050 of these patients have been treated for at least three months and more than 950 patients have been treated for at least six months. The range of patient exposure was from 1 to over 500 days.

Adverse Reactions Leading to Discontinuation

The rate of discontinuation from a controlled clinical trial of ARICEPT 23 mg/day due to adverse reactions was higher (19%) than for the 10 mg/day treatment group (8%). The most common adverse reactions leading to discontinuation, defined as those occurring in at least 1% of patients and greater than those occurring with 10 mg/day are shown in Table 5.

Table 5. Most Common Adverse Reactions Leading to
Discontinuation in Patients with Moderate to Severe
Alzheimer’s Disease
Adverse Reaction | 23 mg/day ARICEPT (n=963) % | 10 mg/day ARICEPT (n=471) %
Vomiting | 3 | 0
Diarrhea | 2 | 0
Nausea | 2 | 0
Dizziness | 1 | 0

The majority of discontinuations due to adverse reactions in the 23 mg group occurred during the first month of treatment.

Most Common Adverse Reactions with ARICEPT 23 mg/day

The most common adverse reactions, defined as those occurring at a frequency of at least 5%, include nausea, diarrhea, vomiting, and anorexia.

Table 6 lists adverse reactions that occurred in at least 2% of patients who received 23 mg/day of ARICEPT and at a higher frequency than those receiving 10 mg/day of ARICEPT in a controlled clinical trial that compared the two doses. In this study, there were no important differences in the type of adverse reactions in patients taking ARICEPT with or without memantine.

Table 6. Adverse Reactions in a Controlled Clinical Trial in Moderate to Severe Alzheimer’s Disease
Adverse Reaction | 23 mg/day ARICEPT (n=963) % | 10 mg/day ARICEPT (n=471) %
Percent of Patients with any Adverse Reaction | 74 | 64
Nausea | 12 | 3
Vomiting | 9 | 3
Diarrhea | 8 | 5
Anorexia | 5 | 2
Dizziness | 5 | 3
Weight Loss | 5 | 3
Headache | 4 | 3
Insomnia | 3 | 2
Urinary Incontinence | 3 | 1
Asthenia | 2 | 1
Contusion | 2 | 0
Fatigue | 2 | 1
Somnolence | 2 | 1

6.2 Postmarketing Experience

The following adverse reactions have been identified during post-approval use of ARICEPT. Because these reactions are reported voluntarily from a population of uncertain size, it is not always possible to reliably estimate their frequency or establish a causal relationship to drug exposure.

Abdominal pain, agitation, aggression, cholecystitis, confusion, convulsions, hallucinations, heart block (all types), hemolytic anemia, hepatitis, hyponatremia, neuroleptic malignant syndrome, pancreatitis, rash, rhabdomyolysis, QTc prolongation, and torsade de pointes.

7 DRUG INTERACTIONS

7.1 Use with Anticholinergics

Because of their mechanism of action, cholinesterase inhibitors have the potential to interfere with the activity of anticholinergic medications.

7.2 Use with Cholinomimetics and Other Cholinesterase Inhibitors

A synergistic effect may be expected when cholinesterase inhibitors are given concurrently with succinylcholine, similar neuromuscular blocking agents, or cholinergic agonists such as bethanechol.

8 USE IN SPECIFIC POPULATIONS

8.1 Pregnancy

Risk Summary

There are no adequate data on the developmental risks associated with the use of ARICEPT in pregnant women. In animal studies, developmental toxicity was not observed when donepezil was administered to pregnant rats and rabbits during organogenesis, but administration to rats during the latter part of pregnancy and throughout lactation resulted in increased stillbirths and decreased offspring survival at clinically relevant doses [see Data]. In the U.S. general population, the estimated background risks of major birth defects and miscarriage in clinically recognized pregnancies are 2% to 4% and 15% to 20%, respectively. The background risks of major birth defects and miscarriage for the indicated population are unknown.

Data

Animal Data

Oral administration of donepezil to pregnant rats and rabbits during the period of organogenesis did not produce any teratogenic effects at doses up to 16 mg/kg/day (approximately 6 times the maximum recommended human dose [MRHD] of 23 mg/day on a mg/m^2 basis) and 10 mg/kg/day (approximately 7 times the MRHD on a mg/m^2 basis), respectively. Oral administration of donepezil (1, 3, 10 mg/kg/day) to rats during late gestation and throughout lactation to weaning produced an increase in stillbirths and reduced offspring survival through postpartum day 4 at the highest dose. The no-effect dose of 3 mg/kg/day is approximately equal to the MRHD on a mg/m^2 basis.

8.2 Lactation

Risk Summary

There are no data on the presence of donepezil or its metabolites in human milk, the effects on the breastfed infant, or on milk production.

The developmental and health benefits of breastfeeding should be considered along with the mother’s clinical need for ARICEPT and any potential adverse effects on the breastfed infant from ARICEPT or from the underlying maternal condition.

8.4 Pediatric Use

The safety and effectiveness in pediatric patients have not been established.

8.5 Geriatric Use

Alzheimer’s disease is a disorder occurring primarily in individuals over 55 years of age. The mean age of patients enrolled in the clinical studies with ARICEPT was 73 years; 80% of these patients were between 65 and 84 years old, and 49% of patients were at or above the age of 75. The efficacy and safety data presented in the clinical trials section were obtained from these patients. There were no clinically significant differences in most adverse reactions reported by patient groups ≥ 65 years old and < 65 years old.

8.6 Lower Weight Individuals

In the controlled clinical trial, among patients in the ARICEPT 23 mg treatment group, those patients weighing < 55 kg reported more nausea, vomiting, and decreased weight than patients weighing 55 kg or more. There were more withdrawals due to adverse reactions as well. This finding may be related to higher plasma exposure associated with lower weight.

10 OVERDOSAGE

Because strategies for the management of overdose are continually evolving, it is advisable to contact a Poison Control Center to determine the latest recommendations for the management of an overdose of any drug.

As in any case of overdose, general supportive measures should be utilized. Overdosage with cholinesterase inhibitors can result in cholinergic crisis characterized by severe nausea, vomiting, salivation, sweating, bradycardia, hypotension, respiratory depression, collapse, and convulsions. Increasing muscle weakness is a possibility and may result in death if respiratory muscles are involved. Tertiary anticholinergics such as atropine may be used as an antidote for ARICEPT overdosage. Intravenous atropine sulfate titrated to effect is recommended: an initial dose of 1.0 to 2.0 mg IV with subsequent doses based upon clinical response. Atypical responses in blood pressure and heart rate have been reported with other cholinomimetics when co-administered with quaternary anticholinergics such as glycopyrrolate. It is not known whether ARICEPT and/or its metabolites can be removed by dialysis (hemodialysis, peritoneal dialysis, or hemofiltration).

Dose-related signs of toxicity in animals included reduced spontaneous movement, prone position, staggering gait, lacrimation, clonic convulsions, depressed respiration, salivation, miosis, tremors, fasciculation, and lower body surface temperature.

11 DESCRIPTION

ARICEPT (donepezil hydrochloride) is a reversible inhibitor of the enzyme acetylcholinesterase, known chemically as (±)-2, 3-dihydro-5, 6-dimethoxy-2-[[1-(phenylmethyl)-4-piperidinyl]methyl]-1H-inden-1-one hydrochloride. Donepezil hydrochloride is commonly referred to in the pharmacological literature as E2020. It has an empirical formula of C24H29NO3HCl and a molecular weight of 415.96. Donepezil hydrochloride is a white crystalline powder and is freely soluble in chloroform, soluble in water and in glacial acetic acid, slightly soluble in ethanol and in acetonitrile, and practically insoluble in ethyl acetate and in n-hexane.

ARICEPT is available for oral administration in film-coated tablets containing 5, 10, or 23 mg of donepezil hydrochloride.

Inactive ingredients in 5 mg and 10 mg tablets are lactose monohydrate, corn starch, microcrystalline cellulose, hydroxypropyl cellulose, and magnesium stearate. The film coating contains talc, polyethylene glycol, hypromellose, and titanium dioxide. Additionally, the 10 mg tablet contains yellow iron oxide (synthetic) as a coloring agent.

Inactive ingredients in 23 mg tablets include ethylcellulose, hydroxypropyl cellulose, lactose monohydrate, magnesium stearate, and methacrylic acid copolymer, Type C. The film coating includes ferric oxide, hypromellose 2910, polyethylene glycol 8000, talc, and titanium dioxide.

ARICEPT ODT tablets are available for oral administration. Each ARICEPT ODT tablet contains 5 or 10 mg of donepezil hydrochloride. Inactive ingredients are carrageenan, mannitol, colloidal silicon dioxide, and polyvinyl alcohol. Additionally, the 10 mg tablet contains ferric oxide (yellow) as a coloring agent.

12 CLINICAL PHARMACOLOGY

12.1 Mechanism of Action

Current theories on the pathogenesis of the cognitive signs and symptoms of Alzheimer’s disease attribute some of them to a deficiency of cholinergic neurotransmission.

Donepezil hydrochloride is postulated to exert its therapeutic effect by enhancing cholinergic function. This is accomplished by increasing the concentration of acetylcholine through reversible inhibition of its hydrolysis by acetylcholinesterase. There is no evidence that donepezil alters the course of the underlying dementing process.

12.3 Pharmacokinetics

Pharmacokinetics of donepezil are linear over a dose range of 1-10 mg given once daily. The rate and extent of absorption of ARICEPT tablets are not influenced by food.

Based on population pharmacokinetic analysis of plasma donepezil concentrations measured in patients with Alzheimer’s disease, following oral dosing, peak plasma concentration is achieved for ARICEPT 23 mg tablets in approximately 8 hours, compared with 3 hours for ARICEPT 10 mg tablets. Peak plasma concentrations were about 2-fold higher for ARICEPT 23 mg tablets than ARICEPT 10 mg tablets.

ARICEPT ODT 5 mg and 10 mg are bioequivalent to ARICEPT 5 mg and 10 mg tablets, respectively. A food effect study has not been conducted with ARICEPT ODT; however, the effect of food with ARICEPT ODT is expected to be minimal. ARICEPT ODT can be taken without regard to meals.

The elimination half life of donepezil is about 70 hours, and the mean apparent plasma clearance (Cl/F) is 0.13-0.19 L/hr/kg. Following multiple dose administration, donepezil accumulates in plasma by 4-7 fold, and steady state is reached within 15 days. The steady state volume of distribution is 12-16 L/kg. Donepezil is approximately 96% bound to human plasma proteins, mainly to albumins (about 75%) and alpha1 - acid glycoprotein (about 21%) over the concentration range of 2-1000 ng/mL.

Donepezil is both excreted in the urine intact and extensively metabolized to four major metabolites, two of which are known to be active, and a number of minor metabolites, not all of which have been identified. Donepezil is metabolized by CYP 450 isoenzymes 2D6 and 3A4 and undergoes glucuronidation. Following administration of ^14C-labeled donepezil, plasma radioactivity, expressed as a percent of the administered dose, was present primarily as intact donepezil (53%) and as 6-O-desmethyl donepezil (11%), which has been reported to inhibit AChE to the same extent as donepezil in vitro and was found in plasma at concentrations equal to about 20% of donepezil. Approximately 57% and 15% of the total radioactivity was recovered in urine and feces, respectively, over a period of 10 days, while 28% remained unrecovered, with about 17% of the donepezil dose recovered in the urine as unchanged drug. Examination of the effect of CYP2D6 genotype in Alzheimer’s patients showed differences in clearance values among CYP2D6 genotype subgroups. When compared to the extensive metabolizers, poor metabolizers had a 31.5% slower clearance and ultra-rapid metabolizers had a 24% faster clearance.

Hepatic Disease
In a study of 10 patients with stable alcoholic cirrhosis, the clearance of ARICEPT was decreased by 20% relative to 10 healthy age- and sex-matched subjects.

Renal Disease
In a study of 11 patients with moderate to severe renal impairment (ClC < 18 mL/min/1.73 m^2) the clearance of ARICEPT did not differ from 11 age- and sex-matched healthy subjects.

Age
No formal pharmacokinetic study was conducted to examine age-related differences in the pharmacokinetics of ARICEPT. Population pharmacokinetic analysis suggested that the clearance of donepezil in patients decreases with increasing age. When compared with 65-year old subjects, 90-year old subjects have a 17% decrease in clearance, while 40-year old subjects have a 33% increase in clearance. The effect of age on donepezil clearance may not be clinically significant.

Gender and Race
No specific pharmacokinetic study was conducted to investigate the effects of gender and race on the disposition of ARICEPT. However, retrospective pharmacokinetic analysis and population pharmacokinetic analysis of plasma donepezil concentrations measured in patients with Alzheimer’s disease indicates that gender and race (Japanese and Caucasians) did not affect the clearance of ARICEPT to an important degree.

Body Weight
There was a relationship noted between body weight and clearance. Over the range of body weight from 50 kg to 110 kg, clearance increased from 7.77 L/h to 14.04 L/h, with a value of 10 L/hr for 70 kg individuals.

Drug Interactions

Effect of ARICEPT on the Metabolism of Other Drugs
No in vivo clinical trials have investigated the effect of ARICEPT on the clearance of drugs metabolized by CYP 3A4 (e.g., cisapride, terfenadine) or by CYP 2D6 (e.g., imipramine). However, in vitro studies show a low rate of binding to these enzymes (mean Ki about 50-130 μM), that, given the therapeutic plasma concentrations of donepezil (164 nM), indicates little likelihood of interference. Based on in vitro studies, donepezil shows little or no evidence of direct inhibition of CYP2B6, CYP2C8, and CYP2C19 at clinically relevant concentrations.

Whether ARICEPT has any potential for enzyme induction is not known. Formal pharmacokinetic studies evaluated the potential of ARICEPT for interaction with theophylline, cimetidine, warfarin, digoxin, and ketoconazole. No effects of ARICEPT on the pharmacokinetics of these drugs were observed.

Effect of Other Drugs on the Metabolism of ARICEPT
Ketoconazole and quinidine, strong inhibitors of CYP450 3A and 2D6, respectively, inhibit donepezil metabolism in vitro. Whether there is a clinical effect of quinidine is not known. Population pharmacokinetic analysis showed that in the presence of concomitant CYP2D6 inhibitors donepezil AUC was increased by approximately 17% to 20% in Alzheimer’s disease patients taking ARICEPT 10 and 23 mg. This represented an average effect of weak, moderate, and strong CYP2D6 inhibitors. In a 7-day crossover study in 18 healthy volunteers, ketoconazole (200 mg q.d.) increased mean donepezil (5 mg q.d.) concentrations (AUC0-24 and Cmax) by 36%. The clinical relevance of this increase in concentration is unknown.

Inducers of CYP 3A (e.g., phenytoin, carbamazepine, dexamethasone, rifampin, and phenobarbital) could increase the rate of elimination of ARICEPT.

Formal pharmacokinetic studies demonstrated that the metabolism of ARICEPT is not significantly affected by concurrent administration of digoxin or cimetidine.

An in vitro study showed that donepezil was not a substrate of P-glycoprotein.

Drugs Highly Bound to Plasma Proteins
Drug displacement studies have been performed in vitro between this highly bound drug (96%) and other drugs such as furosemide, digoxin, and warfarin. ARICEPT at concentrations of 0.3-10 micrograms/mL did not affect the binding of furosemide (5 micrograms/mL), digoxin (2 ng/mL), and warfarin (3 micrograms/mL) to human albumin. Similarly, the binding of ARICEPT to human albumin was not affected by furosemide, digoxin, and warfarin.

13 NONCLINICAL TOXICOLOGY

13.1 Carcinogenesis, Mutagenesis, Impairment of Fertility

No evidence of carcinogenic potential was obtained in an 88-week carcinogenicity study of donepezil conducted in mice at oral doses up to 180 mg/kg/day (approximately 40 times the maximum recommended human dose [MRHD] of 23 mg/day on a mg/m^2 basis), or in a 104-week carcinogenicity study in rats at oral doses up to 30 mg/kg/day (approximately 13 times the MRHD on a mg/m^2 basis).

Donepezil was negative in a battery of genotoxicity assays (in vitro bacterial reverse mutation, in vitro mouse lymphoma tk, in vitro chromosomal aberration, and in vivo mouse micronucleus).

Donepezil had no effect on fertility in rats at oral doses up to 10 mg/kg/day (approximately 4 times the MRHD on a mg/m^2 basis) when administered to males and females prior to and during mating and continuing in females through implantation.

13.2 Animal Toxicology and/or Pharmacology

In an acute dose neurotoxicity study in female rats, oral administration of donepezil and memantine in combination resulted in increased incidence, severity, and distribution of neurodegeneration compared with memantine alone. The no-effect levels of the combination were associated with clinically relevant plasma donepezil and memantine levels.

The relevance of this finding to humans is unknown.

14 CLINICAL STUDIES

14.1 Mild to Moderate Alzheimer’s Disease

The effectiveness of ARICEPT as a treatment for mild to moderate Alzheimer’s disease is demonstrated by the results of two randomized, double-blind, placebo-controlled clinical investigations in patients with Alzheimer’s disease (diagnosed by NINCDS and DSM III-R criteria, Mini-Mental State Examination ≥ 10 and ≤ 26 and Clinical Dementia Rating of 1 or 2). The mean age of patients participating in ARICEPT trials was 73 years with a range of 50 to 94. Approximately 62% of patients were women and 38% were men. The racial distribution was white 95%, black 3%, and other races 2%.

The higher dose of 10 mg did not provide a statistically significantly greater clinical benefit than 5 mg. There is a suggestion, however, based upon order of group mean scores and dose trend analyses of data from these clinical trials, that a daily dose of 10 mg of ARICEPT might provide additional benefit for some patients. Accordingly, whether or not to employ a dose of 10 mg is a matter of prescriber and patient preference.

Study Outcome Measures
In each study, the effectiveness of treatment with ARICEPT was evaluated using a dual outcome assessment strategy.

The ability of ARICEPT to improve cognitive performance was assessed with the cognitive subscale of the Alzheimer’s Disease Assessment Scale (ADAS-cog), a multi-item instrument that has been extensively validated in longitudinal cohorts of Alzheimer’s disease patients. The ADAS-cog examines selected aspects of cognitive performance including elements of memory, orientation, attention, reasoning, language, and praxis. The ADAS-cog scoring range is from 0 to 70, with higher scores indicating greater cognitive impairment. Elderly normal adults may score as low as 0 or 1, but it is not unusual for non-demented adults to score slightly higher.

The patients recruited as participants in each study had mean scores on the ADAS-cog of approximately 26 points, with a range from 4 to 61. Experience based on longitudinal studies of ambulatory patients with mild to moderate Alzheimer’s disease suggest that scores on the ADAS-cog increase (worsen) by 6-12 points per year. However, smaller changes may be seen in patients with very mild or very advanced disease since the ADAS-cog is not uniformly sensitive to change over the course of the disease. The annualized rate of decline in the placebo patients participating in ARICEPT trials was approximately 2 to 4 points per year.

The ability of ARICEPT to produce an overall clinical effect was assessed using a Clinician’s Interview-Based Impression of Change that required the use of caregiver information, the CIBIC-plus. The CIBIC-plus is not a single instrument and is not a standardized instrument like the ADAS-cog. Clinical trials for investigational drugs have used a variety of CIBIC formats, each different in terms of depth and structure.

As such, results from a CIBIC-plus reflect clinical experience from the trial or trials in which it was used and cannot be compared directly with the results of CIBIC-plus evaluations from other clinical trials. The CIBIC-plus used in ARICEPT trials was a semi-structured instrument that was intended to examine four major areas of patient function: General, Cognitive, Behavioral, and Activities of Daily Living. It represents the assessment of a skilled clinician based upon his/her observations at an interview with the patient, in combination with information supplied by a caregiver familiar with the behavior of the patient over the interval rated. The CIBIC-plus is scored as a seven-point categorical rating, ranging from a score of 1, indicating “markedly improved,” to a score of 4, indicating “no change” to a score of 7, indicating “markedly worse.” The CIBIC-plus has not been systematically compared directly to assessments not using information from caregivers (CIBIC) or other global methods.

Thirty-Week Study

In a study of 30 weeks duration, 473 patients were randomized to receive single daily doses of placebo, 5 mg/day or 10 mg/day of ARICEPT. The 30-week study was divided into a 24-week double-blind active treatment phase followed by a 6-week single-blind placebo washout period. The study was designed to compare 5 mg/day or 10 mg/day fixed doses of ARICEPT to placebo. However, to reduce the likelihood of cholinergic effects, the 10 mg/day treatment was started following an initial 7-day treatment with 5 mg/day doses.

Effects on the ADAS-cog
Figure 1 illustrates the time course for the change from baseline in ADAS-cog scores for all three dose groups over the 30 weeks of the study. After 24 weeks of treatment, the mean differences in the ADAS-cog change scores for ARICEPT treated patients compared to the patients on placebo were 2.8 and 3.1 points for the 5 mg/day and 10 mg/day treatments, respectively. These differences were statistically significant. While the treatment effect size may appear to be slightly greater for the 10 mg/day treatment, there was no statistically significant difference between the two active treatments.

Following 6 weeks of placebo washout, scores on the ADAS-cog for both the ARICEPT treatment groups were indistinguishable from those patients who had received only placebo for 30 weeks. This suggests that the beneficial effects of ARICEPT abate over 6 weeks following discontinuation of treatment and do not represent a change in the underlying disease. There was no evidence of a rebound effect 6 weeks after abrupt discontinuation of therapy.

Figure 1. Time-course of the Change from Baseline in ADAS-cog Score for Patients Completing 24 Weeks of Treatment.

Figure 2 illustrates the cumulative percentages of patients from each of the three treatment groups who had attained the measure of improvement in ADAS-cog score shown on the X axis. Three change scores (7-point and 4-point reductions from baseline or no change in score) have been identified for illustrative purposes, and the percent of patients in each group achieving that result is shown in the inset table.

The curves demonstrate that both patients assigned to placebo and ARICEPT have a wide range of responses, but that the active treatment groups are more likely to show greater improvements. A curve for an effective treatment would be shifted to the left of the curve for placebo, while an ineffective or deleterious treatment would be superimposed upon or shifted to the right of the curve for placebo.

Figure 2. Cumulative Percentage of Patients Completing 24 Weeks of Double-blind Treatment with Specified Changes from Baseline ADAS-cog Scores. The Percentages of Randomized Patients who Completed the Study were: Placebo 80%, 5 mg/day 85%, and 10 mg/day 68%.

Effects on the CIBIC-plus
Figure 3 is a histogram of the frequency distribution of CIBIC-plus scores attained by patients assigned to each of the three treatment groups who completed 24 weeks of treatment. The mean drug-placebo differences for these groups of patients were 0.35 points and 0.39 points for 5 mg/day and 10 mg/day of ARICEPT, respectively. These differences were statistically significant. There was no statistically significant difference between the two active treatments.

Figure 3. Frequency Distribution of CIBIC-plus Scores at Week 24.

Fifteen-Week Study

In a study of 15 weeks duration, patients were randomized to receive single daily doses of placebo or either 5 mg/day or 10 mg/day of ARICEPT for 12 weeks, followed by a 3-week placebo washout period. As in the 30-week study, to avoid acute cholinergic effects, the 10 mg/day treatment followed an initial 7-day treatment with 5 mg/day doses.

Effects on the ADAS-cog
Figure 4 illustrates the time course of the change from baseline in ADAS-cog scores for all three dose groups over the 15 weeks of the study. After 12 weeks of treatment, the differences in mean ADAS-cog change scores for the ARICEPT treated patients compared to the patients on placebo were 2.7 and 3.0 points each, for the 5 and 10 mg/day ARICEPT treatment groups, respectively. These differences were statistically significant. The effect size for the 10 mg/day group may appear to be slightly larger than that for 5 mg/day. However, the differences between active treatments were not statistically significant.

Figure 4. Time-course of the Change from Baseline in ADAS-cog Score for Patients Completing the 15-week Study.

Following 3 weeks of placebo washout, scores on the ADAS-cog for both the ARICEPT treatment groups increased, indicating that discontinuation of ARICEPT resulted in a loss of its treatment effect. The duration of this placebo washout period was not sufficient to characterize the rate of loss of the treatment effect, but the 30-week study (see above) demonstrated that treatment effects associated with the use of ARICEPT abate within 6 weeks of treatment discontinuation.

Figure 5 illustrates the cumulative percentages of patients from each of the three treatment groups who attained the measure of improvement in ADAS-cog score shown on the X axis. The same three change scores (7-point and 4-point reductions from baseline or no change in score) as selected for the 30-week study have been used for this illustration. The percentages of patients achieving those results are shown in the inset table.

As observed in the 30-week study, the curves demonstrate that patients assigned to either placebo or to ARICEPT have a wide range of responses, but that the ARICEPT treated patients are more likely to show greater improvements in cognitive performance.

Figure 5. Cumulative Percentage of Patients with Specified Changes from Baseline ADAS-cog Scores. The Percentages of Randomized Patients Within Each Treatment Group Who Completed the Study Were: Placebo 93%, 5 mg/day 90%, and 10 mg/day 82%.

Effects on the CIBIC-plus
Figure 6 is a histogram of the frequency distribution of CIBIC-plus scores attained by patients assigned to each of the three treatment groups who completed 12 weeks of treatment. The differences in mean scores for ARICEPT treated patients compared to the patients on placebo at Week 12 were 0.36 and 0.38 points for the 5 mg/day and 10 mg/day treatment groups, respectively. These differences were statistically significant.

Figure 6. Frequency Distribution of CIBIC-plus Scores at Week 12.

In both studies, patient age, sex, and race were not found to predict the clinical outcome of ARICEPT treatment.

14.2 Moderate to Severe Alzheimer's Disease

The effectiveness of ARICEPT in the treatment of patients with moderate to severe Alzheimer’s disease was established in studies employing doses of 10 mg/day and 23 mg/day. Results of a controlled clinical trial in moderate to severe Alzheimer’s Disease that compared ARICEPT 23 mg once daily to 10 mg once daily suggest that a 23 mg dose of ARICEPT provided additional benefit.

Swedish 6 Month Study (10 mg/day)

The effectiveness of ARICEPT as a treatment for severe Alzheimer’s disease is demonstrated by the results of a randomized, double-blind, placebo-controlled clinical study conducted in Sweden (6 month study) in patients with probable or possible Alzheimer’s disease diagnosed by NINCDS-ADRDA and DSM-IV criteria, MMSE: range of 1-10. Two hundred and forty eight (248) patients with severe Alzheimer’s disease were randomized to ARICEPT or placebo. For patients randomized to ARICEPT, treatment was initiated at 5 mg once daily for 28 days and then increased to 10 mg once daily. At the end of the 6 month treatment period, 90.5% of the ARICEPT treated patients were receiving the 10 mg/day dose. The mean age of patients was 84.9 years, with a range of 59 to 99. Approximately 77% of patients were women, and 23% were men. Almost all patients were Caucasian. Probable Alzheimer’s disease was diagnosed in the majority of the patients (83.6% of ARICEPT treated patients and 84.2% of placebo treated patients).

Study Outcome Measures
The effectiveness of treatment with ARICEPT was determined using a dual outcome assessment strategy that evaluated cognitive function using an instrument designed for more impaired patients and overall function through caregiver-rated assessment. This study showed that patients on ARICEPT experienced significant improvement on both measures compared to placebo.

The ability of ARICEPT to improve cognitive performance was assessed with the Severe Impairment Battery (SIB). The SIB, a multi-item instrument, has been validated for the evaluation of cognitive function in patients with moderate to severe dementia. The SIB evaluates selective aspects of cognitive performance, including elements of memory, language, orientation, attention, praxis, visuospatial ability, construction, and social interaction. The SIB scoring range is from 0 to 100, with lower scores indicating greater cognitive impairment.

Daily function was assessed using the Modified Alzheimer’s Disease Cooperative Study Activities of Daily Living Inventory for Severe Alzheimer’s Disease (ADCS-ADL-severe). The ADCS-ADL-severe is derived from the Alzheimer’s Disease Cooperative Study Activities of Daily Living Inventory, which is a comprehensive battery of ADL questions used to measure the functional capabilities of patients. Each ADL item is rated from the highest level of independent performance to complete loss. The ADCS-ADL-severe is a subset of 19 items, including ratings of the patient’s ability to eat, dress, bathe, use the telephone, get around (or travel), and perform other activities of daily living; it has been validated for the assessment of patients with moderate to severe dementia. The ADCS-ADL-severe has a scoring range of 0 to 54, with the lower scores indicating greater functional impairment. The investigator performs the inventory by interviewing a caregiver, in this study a nurse staff member, familiar with the functioning of the patient.

Effects on the SIB
Figure 7 shows the time course for the change from baseline in SIB score for the two treatment groups over the 6 months of the study. At 6 months of treatment, the mean difference in the SIB change scores for ARICEPT treated patients compared to patients on placebo was 5.9 points. ARICEPT treatment was statistically significantly superior to placebo.

Figure 7. Time Course of the Change from Baseline in SIB Score for Patients Completing 6 Months of Treatment.

Figure 8 illustrates the cumulative percentages of patients from each of the two treatment groups who attained the measure of improvement in SIB score shown on the X-axis. While patients assigned both to ARICEPT and to placebo have a wide range of responses, the curves show that the ARICEPT group is more likely to show a greater improvement in cognitive performance.

Figure 8. Cumulative Percentage of Patients Completing 6 Months of Double-blind Treatment with Particular Changes from Baseline in SIB Scores.
Figure 9. Time Course of the Change from Baseline in ADCS-ADL-Severe Score for Patients Completing 6 Months of Treatment.

Effects on the ADCS-ADL-severe
Figure 9 illustrates the time course for the change from baseline in ADCS-ADL-severe scores for patients in the two treatment groups over the 6 months of the study. After 6 months of treatment, the mean difference in the ADCS-ADL-severe change scores for ARICEPT treated patients compared to patients on placebo was 1.8 points. ARICEPT treatment was statistically significantly superior to placebo.

Figure 10 shows the cumulative percentages of patients from each treatment group with specified changes from baseline ADCS-ADL-severe scores. While both patients assigned to ARICEPT and placebo have a wide range of responses, the curves demonstrate that the ARICEPT group is more likely to show a smaller decline or an improvement.

Figure 10. Cumulative Percentage of Patients Completing 6 Months of Double-blind Treatment with Particular Changes from Baseline in ADCS-ADL-Severe Scores.

Japanese 24-Week Study (10 mg/day)

In a study of 24 weeks duration conducted in Japan, 325 patients with severe Alzheimer’s disease were randomized to doses of 5 mg/day or 10 mg/day of donepezil, administered once daily, or placebo. Patients randomized to treatment with donepezil were to achieve their assigned doses by titration, beginning at 3 mg/day, and extending over a maximum of 6 weeks. Two hundred and forty eight (248) patients completed the study, with similar proportions of patients completing the study in each treatment group. The primary efficacy measures for this study were the SIB and CIBIC-plus.

At 24 weeks of treatment, statistically significant treatment differences were observed between the 10 mg/day dose of donepezil and placebo on both the SIB and CIBIC-plus. The 5 mg/day dose of donepezil showed a statistically significant superiority to placebo on the SIB, but not on the CIBIC-plus.

Study of 23 mg/day

The effectiveness of ARICEPT 23 mg/day as a treatment for moderate to severe Alzheimer’s disease has been demonstrated by the results of a randomized, double-blind, controlled clinical investigation in patients with moderate to severe Alzheimer’s disease. The controlled clinical study was conducted globally in patients with probable Alzheimer’s disease diagnosed by NINCDS-ADRDA and DSM-IV criteria, MMSE: range of 0-20. Patients were required to have been on a stable dose of ARICEPT 10 mg/day for at least 3 months prior to screening. One thousand four hundred and thirty four (1434) patients with moderate to severe Alzheimer’s disease were randomized to 23 mg/day or 10 mg/day. The mean age of patients was 73.8 years, with a range of 47 to 90. Approximately 63% of patients were women, and 37% were men. Approximately 36% of the patients were taking memantine throughout the study.

Study Outcome Measures
The effectiveness of treatment with 23 mg/day was determined using a dual outcome assessment strategy that evaluated cognitive function using an instrument designed for more impaired patients and overall function through caregiver-rated assessment.

The ability of 23 mg/day to improve cognitive performance was assessed with the Severe Impairment Battery (SIB). The SIB, a multi-item instrument, has been validated for the evaluation of cognitive function in patients with moderate to severe dementia. The SIB evaluates selective aspects of cognitive performance, including elements of memory, language, orientation, attention, praxis, visuospatial ability, construction, and social interaction. The SIB scoring range is from 0 to 100, with lower scores indicating greater cognitive impairment.

The ability of 23 mg/day to produce an overall clinical effect was assessed using a Clinician’s Interview-Based Impression of Change that incorporated the use of caregiver information, the CIBIC-plus. The CIBIC-plus used in this trial was a semi-structured instrument that examines four major areas of patient function: General, Cognitive, Behavioral, and Activities of Daily Living. It represents the assessment of a skilled clinician based upon his/her observations at an interview with the patient, in combination with information supplied by a caregiver familiar with the behavior of the patient over the interval rated. The CIBIC-plus is scored as a seven-point categorical rating, ranging from a score of 1, indicating “markedly improved,” to a score of 4, indicating “no change” to a score of 7, indicating “markedly worse.”

Effects on the SIB
Figure 11 shows the time course for the change from baseline in SIB score for the two treatment groups over the 24 weeks of the study. At 24 weeks of treatment, the LS mean difference in the SIB change scores for 23 mg/day-treated patients compared to patients treated with 10 mg was 2.2 units (p = 0.0001). The dose of 23 mg/day was statistically significantly superior to the dose of 10 mg/day.

Figure 11. Time-course of the Change from Baseline in SIB Score for Patients Completing 24 Weeks of Treatment.

Figure 12 illustrates the cumulative percentages of patients from each of the two treatment groups who attained the measure of improvement in SIB score shown on the X-axis. While patients assigned both to 23 mg/day and to 10 mg/day have a wide range of responses, the curves show that the 23 mg-group is more likely to show a greater improvement in cognitive performance. When such curves are shifted to the left, this indicates a greater percentage of patients responding to treatment on the SIB.

Figure 12. Cumulative Percentage of Patients Completing 24 Weeks of Double-blind Treatment with Specified Changes from Baseline SIB Scores.

Effects on the CIBIC-plus
Figure 13 is a histogram of the frequency distribution of CIBIC-plus scores attained by patients at the end of 24 weeks of treatment. The mean difference between the 23 mg/day and 10 mg/day treatment groups was 0.06 units. This difference was not statistically significant.

Figure 13. Frequency Distribution of CIBIC-plus Scores at Week 24.

16 HOW SUPPLIED/STORAGE AND HANDLING

16.1 ARICEPT Tablets

Supplied as film-coated, round tablets containing 5 mg, 10 mg, or 23 mg of donepezil hydrochloride.

The 5 mg tablets are white. The strength, in mg (5), is debossed on one side and ARICEPT is debossed on the other side.

- Bottles of 30 (NDC# 62856-245-30)
- Bottles of 90 (NDC# 62856-245-90)
- Unit Dose Blister Package 100 (10x10) (NDC# 62856-245-41)

The 10 mg tablets are yellow. The strength, in mg (10), is debossed on one side and ARICEPT is debossed on the other side.

- Bottles of 30 (NDC# 62856-246-30)
- Bottles of 90 (NDC# 62856-246-90)
- Unit Dose Blister Package 100 (10x10) (NDC# 62856-246-41)

The 23 mg tablets are reddish in color. The strength, in mg (23), is debossed on one side and ARICEPT is debossed on the other side.

- Bottles of 30 (NDC# 62856-247-30)

16.2 ARICEPT ODT

Supplied as round tablets containing either 5 mg or 10 mg of donepezil hydrochloride.

The 5 mg orally disintegrating tablets are white. The strength, in mg (5), is debossed on one side and ARICEPT is debossed on the other side.

- 5 mg (White) Unit Dose Blister Package 30 (10x3) (NDC# 62856-831-30)

The 10 mg orally disintegrating tablets are yellow. The strength, in mg (10), is debossed on one side and ARICEPT is debossed on the other side.

- 10 mg (Yellow) Unit Dose Blister Package 30 (10x3) (NDC# 62856-832-30)

Storage
Store at controlled room temperature, 15ºC to 30ºC (59ºF to 86ºF).

17 PATIENT COUNSELING INFORMATION

Advise the patient to read the FDA-approved patient labeling (Patient Information).

Instruct patients and caregivers to take ARICEPT only once per day, as prescribed.

Instruct patients and caregivers that ARICEPT can be taken with or without food. ARICEPT 23 mg tablets should be swallowed whole without the tablets being split, crushed or chewed. ARICEPT ODT should not be swallowed whole, but be allowed to dissolve on the tongue and followed with water.

Advise patients and caregivers that ARICEPT may cause nausea, diarrhea, insomnia, vomiting, muscle cramps, fatigue, and decreased appetite.

Advise patients to notify their healthcare provider if they are pregnant or plan to become pregnant.

ARICEPT PATIENT PACKAGE INSERT

ARICEPT® (Air-eh-sept)

(donepezil hydrochloride) tablets

- Tablets: 5 mg, 10 mg, and 23 mg

ARICEPT® ODT (Air-eh-sept oh-dee-tee)

(donepezil hydrochloride) orally disintegrating tablets

- ODT Tablets: 5 mg and 10 mg

Read this Patient Information that comes with ARICEPT before you start taking it and each time you get a refill. There may be new information. This leaflet does not take the place of talking with your doctor about Alzheimer’s disease or treatment for it. If you have questions, ask the doctor or pharmacist.

What is ARICEPT?

ARICEPT comes as ARICEPT film-coated tablets in dosage strengths of 5 mg, 10 mg, and 23 mg, and as ARICEPT Orally Disintegrating Tablets (ODT; 5 mg and 10 mg). Except where indicated, all the information about ARICEPT in this leaflet also applies to ARICEPT ODT.

ARICEPT is a prescription medicine to treat mild, moderate, and severe Alzheimer’s disease. ARICEPT can help with mental function and with doing daily tasks. ARICEPT does not work the same in all people. Some people may:

- Seem much better
- Get better in small ways or stay the same
- Get worse over time but slower than expected
- Not change and then get worse as expected

ARICEPT does not cure Alzheimer’s disease. All patients with Alzheimer’s disease get worse over time, even if they take ARICEPT.

ARICEPT has not been approved as a treatment for any medical condition in children.

Who should not take ARICEPT?

Do not take ARICEPT if you are allergic to any of the ingredients in ARICEPT or to medicines that contain piperidines. Ask your doctor if you are not sure. See the end of this leaflet for a list of ingredients in ARICEPT.

What should I tell my doctor before taking ARICEPT?

Tell the doctor about all of your present or past health problems and conditions. Include:

- Any heart problems including problems with irregular, slow, or fast heartbeats
- Asthma or lung problems
- A seizure
- Stomach ulcers
- Difficulty passing urine
- Liver or kidney problems
- Trouble swallowing tablets
- Present pregnancy or plans to become pregnant. It is not known if ARICEPT can harm an unborn baby.
- Present breast-feeding. It is not known if ARICEPT passes into breast milk. Talk to your doctor about the best way to feed your baby if you take ARICEPT.

Tell the doctor about all the medicines you take, including prescription and non-prescription medicines, vitamins, and herbal products. ARICEPT and other medicines may affect each other.

Be particularly sure to tell the doctor if you take aspirin or medicines called nonsteroidal anti-inflammatory drugs (NSAIDs). There are many NSAID medicines, both prescription and non-prescription. Ask the doctor or pharmacist if you are not sure if any of your medicines are NSAIDs. Taking NSAIDs and ARICEPT together may make you more likely to get stomach ulcers.

ARICEPT taken with certain medicines used for anesthesia may cause side effects. Tell the responsible doctor or dentist that you take ARICEPT before you have:

- surgery
- medical procedures
- dental surgery or procedures.

Know the medicines that you take. Keep a list of all your medicines. Show it to your doctor or pharmacist before you start a new medicine.

How should you take ARICEPT?

- Take ARICEPT exactly as prescribed by the doctor. Do not stop ARICEPT or change the dose yourself. Talk with your doctor first.
- Take ARICEPT one time each day. ARICEPT can be taken with or without food.
- ARICEPT 23 mg tablets should be swallowed whole. Do not split, crush, or chew the tablets.
- ARICEPT ODT melts on the tongue. You should drink some water after the tablet melts.
- If you miss a dose of ARICEPT, just wait. Take only the next dose at the usual time. Do not take 2 doses at the same time.
- If ARICEPT is missed for 7 days or more, talk with your doctor before starting again.
- If you take too much ARICEPT at one time, call your doctor or poison control center, or go to the emergency room right away.

What are the possible side effects of ARICEPT?

ARICEPT may cause the following serious side effects:

- slow heartbeat and fainting. This happens more often in people with heart problems. Call your doctor right away if you feel faint or lightheaded while taking ARICEPT.
- more stomach acid. This raises the chance of ulcers and bleeding, especially when taking ARICEPT 23 mg. The risk is higher for people who have had ulcers, or take aspirin or other NSAIDs.
- worsening of lung problems in people with asthma or other lung disease.
- seizures.
- difficulty passing urine.

Call your doctor right away if you have:

- fainting.
- heartburn or stomach pain that is new or won’t go away.
- nausea or vomiting, blood in the vomit, dark vomit that looks like coffee grounds.
- bowel movements or stools that look like black tar.
- new or worse asthma or breathing problems.
- seizures.
- difficulty passing urine.

The most common side effects of ARICEPT are:

- nausea
- diarrhea
- not sleeping well
- vomiting
- muscle cramps
- feeling tired
- not wanting to eat

These side effects may get better after you take ARICEPT for a while. This is not a complete list of side effects with ARICEPT. For more information, ask your doctor or pharmacist.

Call your doctor for medical advice about side effects. You may report side effects to FDA at 1-800-FDA-1088.

How should ARICEPT be stored?

Store ARICEPT at room temperature between 59º to 86ºF (15º to 30ºC).

Keep ARICEPT and all medicines out of the reach of children.

General information about ARICEPT
Medicines are sometimes prescribed for conditions that are not mentioned in this Patient Information Leaflet. Do not use ARICEPT for a condition for which it was not prescribed. Do not give ARICEPT to other people, even if they have the same symptoms or condition. It may harm them.

This leaflet summarizes the most important information about ARICEPT. If you would like more information, talk with your doctor. You can ask your pharmacist or doctor for information about ARICEPT that is written for health professionals. For more information, go to www.ARICEPT.com, or call 1-800-760-6029.

What are the ingredients in ARICEPT?

Active ingredient: donepezil hydrochloride

Inactive ingredients:

- ARICEPT 5 mg and 10 mg film-coated tablets: lactose monohydrate, cornstarch, microcrystalline cellulose, hydroxypropyl cellulose, and magnesium stearate. The film coating contains talc, polyethylene glycol, hypromellose, and titanium dioxide. Additionally, the 10 mg tablet contains yellow iron oxide (synthetic) as a coloring agent.
- ARICEPT 23 mg film-coated tablets: ethylcellulose, hydroxypropyl cellulose, lactose monohydrate, magnesium stearate, and methacrylic acid copolymer, Type C. The reddish color film coating includes ferric oxide, hypromellose 2910, polyethylene glycol 8000, talc, and titanium dioxide.
- ARICEPT ODT 5 mg and 10 mg tablets: carrageenan, mannitol, colloidal silicon dioxide, and polyvinyl alcohol. The 10 mg tablet contains yellow iron oxide (synthetic) as a coloring agent.

ARICEPT® is a registered trademark used by Eisai Inc. under license from
Eisai R&D Management Co., Ltd.

Distributed by Eisai Inc., Nutley, NJ 07110

Rx Only

© 1996-2021 Eisai Inc.

Revised: 12/2021

PACKAGE LABEL

PRINCIPAL DISPLAY PANEL - ARICEPT 5 MG TABLETS

NDC 62856-245-30

Aricept®
donepezil HCl tablet

5 mg
30 Tablets

PACKAGE LABEL

PRINCIPAL DISPLAY PANEL - ARICEPT 10 MG TABLETS

NDC 62856-246-30

Aricept®
donepezil HCl tablet

10 mg
30 Tablets

PACKAGE LABEL

PRINCIPAL DISPLAY PANEL - ARICEPT 23 MG TABLETS

NDC 62856-247-30

Aricept®
donepezil HCl tablet

23 mg
30 tablets

PACKAGE LABEL

PRINCIPAL DISPLAY PANEL - ARICEPT ODT 5 MG TABLETS

NDC 62856-831-30

ARICEPT® ODT™
(donepezil HCl) 5 MG
orally disintegrating tablets

PACKAGE LABEL

PRINCIPAL DISPLAY PANEL - ARICEPT ODT 10 MG TABLETS

NDC 62856-832-30

ARICEPT® ODT™
(donepezil HCl) 10 MG
orally disintegrating tablets